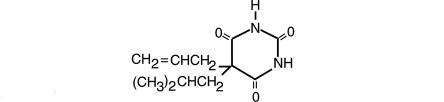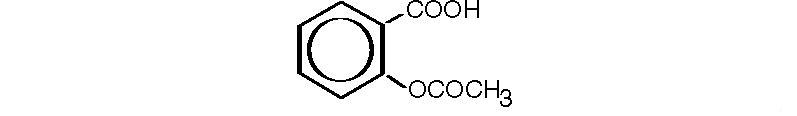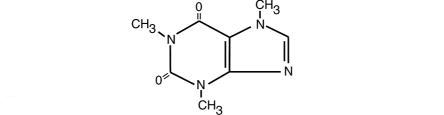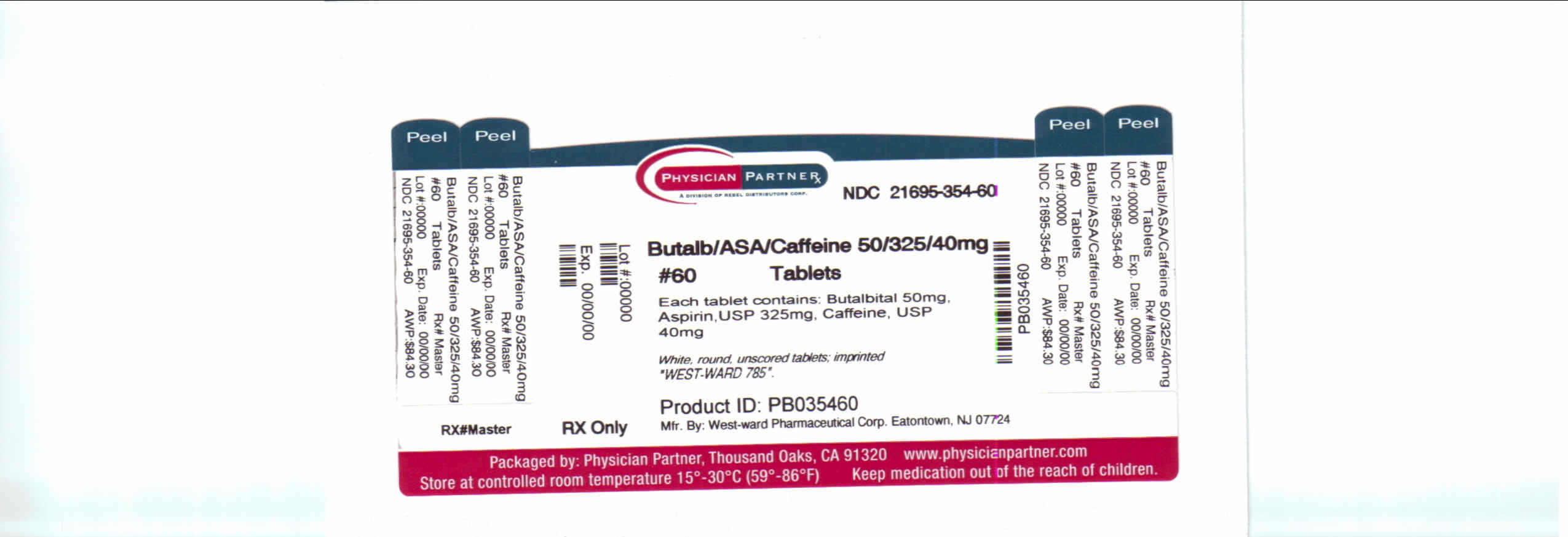 DRUG LABEL: Butalbital, Aspirin and Caffeine
NDC: 21695-354 | Form: TABLET
Manufacturer: Rebel Distributors Corp
Category: prescription | Type: HUMAN PRESCRIPTION DRUG LABEL
Date: 20101210
DEA Schedule: CIII

ACTIVE INGREDIENTS: BUTALBITAL 50 mg/1 1; ASPIRIN 325 mg/1 1; CAFFEINE 40 mg/1 1
INACTIVE INGREDIENTS: STARCH, CORN; CELLULOSE, MICROCRYSTALLINE; TALC

Butalbital, Aspirin, and Caffeine Tablets, USP CIII
Rev. 04/03
Rx Only

DESCRIPTION:

Each Butalbital, Aspirin, and Caffeine Tablet for oral administration contains:

Butalbital, USP.....................50 mg

Aspirin, USP.......................325 mg

Caffeine, USP.......................40 mg

Butalbital, 5-allyl-5-isobutylbarbituric acid, a white, odorless, crystalline powder having a slightly bitter taste, is a short to intermediate-acting barbiturate. It has the following structural formula:

C11H16N2O3 M.W. 224.26

Aspirin, salicylic acid acetate, is a non-opiate analgesic, anti-inflammatory and antipyretic agent. It occurs as a white, crystalline tabular or needle-like powder and is odorless or has a faint odor. It has the following structural formula:

C9H8O4 M.W. 180.16

Caffeine, 1,3,7,-trimethylxanthine, is a central nervous system stimulant which occurs as a white powder or white glistening needles. It also has a bitter taste. Its structure is as follows:

C8H10N4O2 M.W. 194.19

Inactive Ingredients: Corn Starch, Hydrogenated Vegetable Oil, Microcrystalline Cellulose, Pregelatinized Starch, Sodium Starch Glycolate and Talc.

CLINICAL PHARMACOLOGY:

Pharmacologically, Butalbital, Aspirin, and Caffeine Tablets combine the analgesic properties of aspirin with the anxiolytic and muscle relaxant properties of butalbital.

The clinical effectiveness of a product containing butalbital, aspirin, and caffeine in tension headache has been established in double-blind, placebo-controlled, multiclinic trials. A factorial design study compared the combination product with each of its major components. This study demonstrated that each component contributes to the efficacy of the combination product in the treatment of the target symptoms of tension headache (headache pain, psychic tension, and muscle contraction in the head, neck, and shoulder region). For each symptom and the symptom complex as a whole, the product containing butalbital, aspirin, and caffeine was shown to have significantly superior clinical effects to either of the major components alone.

INDICATIONS AND USAGE:

Butalbital, Aspirin and Caffeine Tablets are indicated for the relief of the symptom complex of tension (or muscle contraction) headache.

CONTRAINDICATIONS:

Hypersensitivity to aspirin, caffeine or barbiturates. Patients with porphyria.

PRECAUTIONS:

1. General:

Butalbital, Aspirin, and Caffeine Tablets should be used with caution in patients with certain medical problems, including those with a history of asthma, allergies and nasal polyps. Also, the drug must be prescribed carefully for patients with hemophilia or other bleeding problems, peptic ulcer, renal impairment, or a history of drug abuse or dependence.

2. Information for Patients:

Butalbital, Aspirin, and Caffeine Tablets may impair the mental and/or physical abilities required for the performance of potentially hazardous tasks, such as driving a car or operating machinery. The patient should be cautioned accordingly.

3. Drug Interactions:

Patients receiving narcotic analgesics, antipsychotics, antianxiety agents, or other CNS depressants (including alcohol) concomitantly with Butalbital, Aspirin, and Caffeine Tablets may exhibit additive CNS depressant effects. When combined therapy is contemplated, the dose of one or both agents should be reduced.

DRUGS | EFFECT
Aspirin w/anti-inflammatory agents | Increased ulcerogenic effects.
Butalbital w/coumarin anticoagulants | Decreased effect of anticoagulant because of increased metabolism resulting from enzyme induction.
Butalbital w/tricyclic antidepressants | Decreased blood levels of the antidepressant.

4. Usage in Pregnancy:

Adequate studies have not been performed in animals to determine whether this drug affects fertility in males or females, has teratogenic potential or has other adverse effects on the fetus. While there are no well-controlled studies in pregnant women, over twenty years of marketing and clinical experience does not include any positive evidence of adverse effects on the fetus. Although there is no clearly defined risk, such experience cannot exclude the possibility of infrequent or subtle damage to the human fetus. Butalbital, Aspirin, and Caffeine Tablets should be used in pregnant women only when clearly needed.

5. Nursing Mothers:

The effects of Butalbital, Aspirin, and Caffeine Tablets on infants of nursing mothers are not known. Salicylates and barbiturates are excreted in the breast milk of nursing mothers. The serum levels in infants are believed to be insignificant with therapeutic doses.

6. Pediatric Use:

Safety and effectiveness in children below the age of 12 have not been established.

ADVERSE REACTIONS:

The most frequent adverse reactions are drowsiness and dizziness. Less frequent adverse reactions are lightheadedness and gastrointestinal disturbances including nausea, vomiting, and flatulence. Mental confusion or depression can occur due to intolerance or overdosage of butalbital.

Several cases of dermatological reactions including toxic epidermal necrolysis and erythema multiforme have been reported.

DRUG ABUSE AND DEPENDENCE:

Butalbital, Aspirin, and Caffeine Tablets are classified as a Schedule III controlled substance.

Prolonged use of barbiturates can produce drug dependence, characterized by psychic dependence, and less frequently, physical dependence and tolerance. The abuse liability of Butalbital, Aspirin, and Caffeine Tablets are similar to that of other barbiturate-containing drug combinations. Caution should be exercised when prescribing medication for patients with a known propensity for taking excessive quantities of drugs, which is not uncommon in patients with chronic tension headache.

OVERDOSAGE:

Symptoms: The toxic effects of acute overdosage of Butalbital, Aspirin, and Caffeine Tablets are attributable mainly to its barbiturate component, and, to a lesser extent, aspirin. Because toxic effects of caffeine occur in very high dosages only, the possibility of significant caffeine toxicity from Butalbital, Aspirin, and Caffeine Tablet overdosage in unlikely. Symptoms attributable to acute barbiturate poisoning include drowsiness, confusion, and coma; respiratory depression; hypotension; shock. Symptoms attributable to acute aspirin poisoning include hyperpnea; acid-base disturbances with development of metabolic acidosis; vomiting and abdominal pain; tinnitus; hyperthermia; hypoprothrombinemia; restlessness; delirium; convulsions. Acute caffeine poisoning may cause insomnia, restlessness, tremor, and delirium; tachycardia and extrasystoles.

Treatment: Treatment consists primarily of management of barbiturate intoxication and the correction of the acid-base imbalance due to salicylism. Vomiting should be induced mechanically or with emetics in the conscious patient. Gastric lavage may be used if the pharyngeal and laryngeal reflexes are present and if less than four hours have elapsed since ingestion. A cuffed endotracheal tube should be inserted before gastric lavage of the unconscious patient and when necessary to provide assisted respiration. Diuresis, alkalinization of the urine, and correction of electrolyte disturbances should be accomplished through administration of intravenous fluids such as 1% sodium bicarbonate in 5% dextrose injection. Meticulous attention should be given to maintaining adequate pulmonary ventilation. Correction of hypotension may require the administration of norepinephrine bitartrate of phenylephrine hydrochloride by intravenous infusion. In severe cases of intoxication, peritoneal dialysis, hemodialysis, or exchange transfusion may be lifesaving. Hypoprothrombinemia should be treated with Vitamin K, intravenously.

DOSAGE AND ADMINISTRATION:

Oral: One or two tablets every four hours as needed. Do not exceed 6 tablets per day.

Medication should be taken with food or a full glass of water or milk to lessen gastric irritation caused by aspirin.

HOW SUPPLIED:

Butalbital, Aspirin and Caffeine Tablets, USP 50 mg/325 mg/40 mg: White, round, unscored tablets; imprinted “West-ward 785”.

Bottles of 60 tablets, NDC 21695-354-60.

Store at 20-25°C (68-77°F) [See USP Controlled Room Temperature]. Protect from light and moisture.

Dispense in a tight, light-resistant container as defined in the USP using a child-resistant closure.

Manufactured By:
West-ward Pharmaceutical Corp.
Eatontown, NJ 07724
Revised April 2003

Repackaged by:

Rebel Distributors Corp

Thousand Oaks, CA 91320